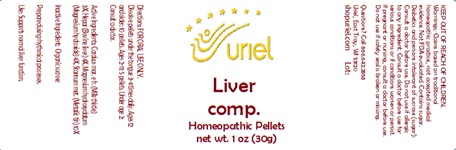 DRUG LABEL: Liver comp.
NDC: 48951-6083 | Form: PELLET
Manufacturer: Uriel Pharmacy Inc.
Category: homeopathic | Type: HUMAN OTC DRUG LABEL
Date: 20241211

ACTIVE INGREDIENTS: MILK THISTLE 3 [hp_X]/1 1; MAMMAL LIVER 4 [hp_X]/1 1; MAGNESIUM HYDROXIDE 4 [hp_X]/1 1; TIN 10 [hp_X]/1 1
INACTIVE INGREDIENTS: SUCROSE

Liver comp.

INDICATIONS AND USAGE

Directions: FOR ORAL USE ONLY.

DOSAGE AND ADMINISTRATION

Dissolve pellets under the tongue 3-4 times daily. Ages 12 and older: 10 pellets. Ages 2-11: 5 pellets. Under age 2: Consult a doctor.

Active Ingredients: Carduus mar. (Milk thistle)
3X, Hepar (Bovine liver) 4X, Magnesium hydroxydatum (Magnesium hydroxide) 4X, Stannum met. (Metallic tin) 10X

Inactive Ingredient: Organic sucrose

Prepared using rhythmical processes.

PURPOSE

Use: Supports normal liver function.

KEEP OUT OF REACH OF CHILDREN.

WARNINGS

Warnings: Claims based on traditional homeopathic practice, not accepted medical evidence. Not FDA evaluated. Contains sugar. Diabetics and persons intolerant of sucrose (sugar): Consult a doctor before use. Do not use if allergic to any ingredient. Consult a doctor before use for serious conditions or if conditions worsen or persist. If pregnant or nursing, consult a doctor before use. Do not use if safety seal is broken or missing.

QUESTIONS

Questions? Call 866.642.2858 Uriel, East Troy, WI 53120 shopuriel.com Lot: